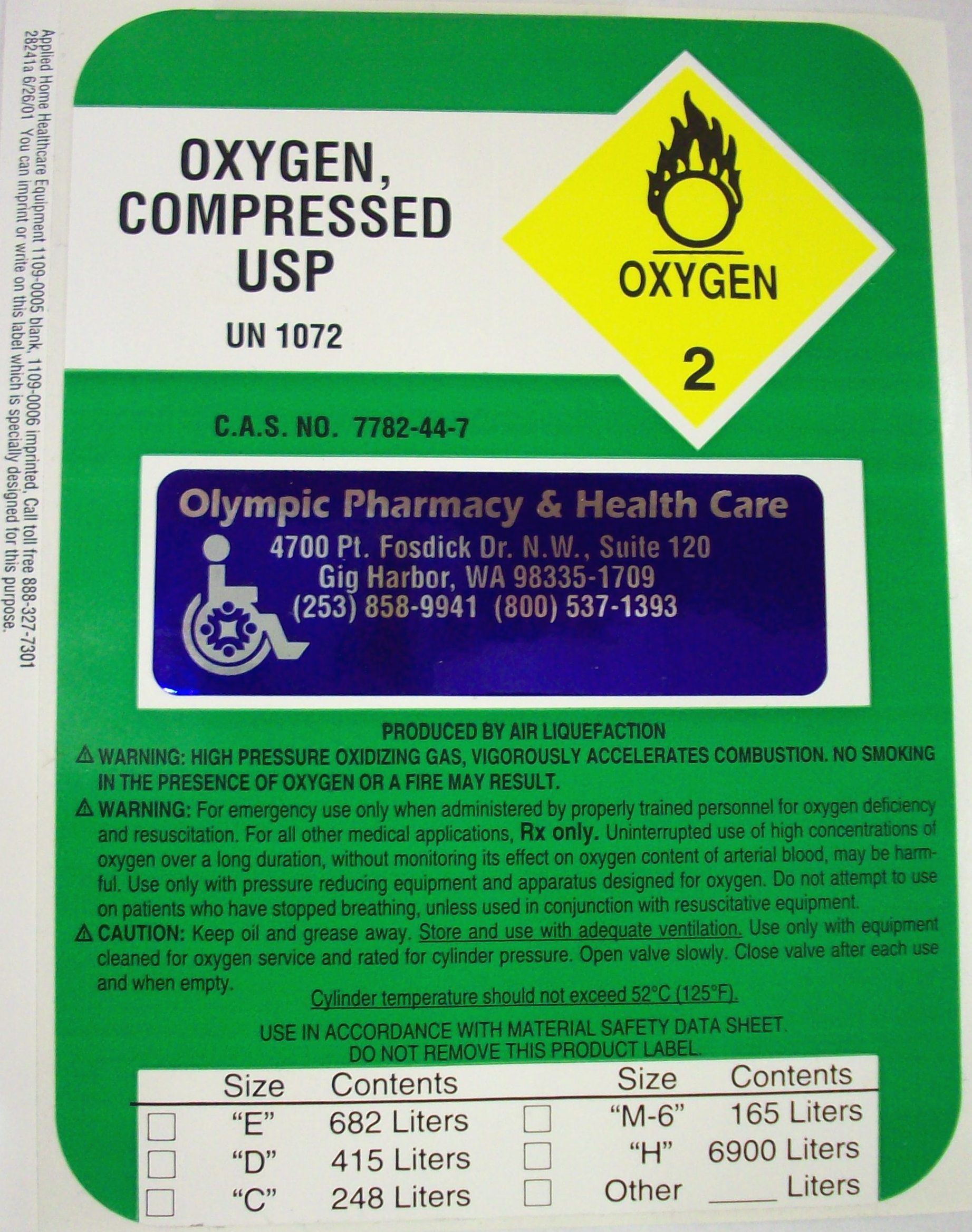 DRUG LABEL: oxygen
NDC: 63234-001 | Form: GAS
Manufacturer: Olympic Pharmacy and Healthcare Services
Category: prescription | Type: HUMAN PRESCRIPTION DRUG LABEL
Date: 20170911

ACTIVE INGREDIENTS: OXYGEN 99.4 L/100 L

PACKAGE LABEL

Oxygen

OXYGEN, COMPRESSED USP
UN 1072
C.A.S. NO. 7782-44-7

PRODUCED BY AIR LIQUEFACTION

WARNING: HIGH PRESSURE OXIDIZING GAS, VIGOROUSLY ACCELERATES COMBUSTION. NO SMOKING IN THE PRESENCE OF OXYGEN OR A FIRE MAY RESULT.
WARNING:

For emergency use only when administered by properly trained personnel for oxygen deficiency and resuscitation. For all other medical applications,

Rx only

. Uninterrupted use of high concentrations of oxygen over a long duration, without monitoring its effect on oxygen content of arterial blood, may be harmful. Use only with pressure reducing equipment and apparatus designed for oxygen. Do not attempt to use on patients who have stopped breathing, unless use in conjunction with resuscitative equipment.

CAUTION:

Keep oil and grease away.

Store and use with adequate ventilation

. Use only with equipment cleaned for oxygen service and rated for cylinder pressure. Open valve slowly. Close valve after each use and when empty.
Cylinder temperature should not exceed 52oC (125oF).
USE IN ACCORDANCE WITH MATERIAL SAFETY DATA SHEET.
DO NOT REMOVE THIS PRODUCT LABEL.